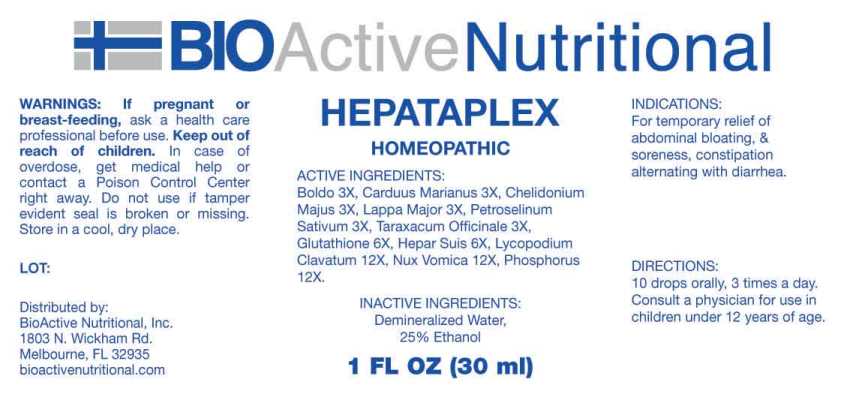 DRUG LABEL: Hepataplex
NDC: 43857-0627 | Form: LIQUID
Manufacturer: BioActive Nutritional, Inc.
Category: homeopathic | Type: HUMAN OTC DRUG LABEL
Date: 20240829

ACTIVE INGREDIENTS: PEUMUS BOLDUS LEAF 3 [hp_X]/1 mL; MILK THISTLE 3 [hp_X]/1 mL; CHELIDONIUM MAJUS WHOLE 3 [hp_X]/1 mL; ARCTIUM LAPPA ROOT 3 [hp_X]/1 mL; PETROSELINUM CRISPUM WHOLE 3 [hp_X]/1 mL; TARAXACUM OFFICINALE 3 [hp_X]/1 mL; GLUTATHIONE 6 [hp_X]/1 mL; PORK LIVER 6 [hp_X]/1 mL; LYCOPODIUM CLAVATUM SPORE 12 [hp_X]/1 mL; STRYCHNOS NUX-VOMICA SEED 12 [hp_X]/1 mL; PHOSPHORUS 12 [hp_X]/1 mL
INACTIVE INGREDIENTS: WATER; ALCOHOL

DRUG FACTS:

ACTIVE INGREDIENTS:

Boldo 3X, Carduus Marianus 3X, Chelidonium Majus 3X, Lappa Major 3X, Petroselinum Sativum 3X, Taraxacum Officinale 3X, Glutathione 6X, Hepar Suis 6X, Lycopodium Clavatum 12X, Nux Vomica 12X, Phosphorus 12X.

INDICATIONS:

For temporary relief of abdominal bloating, & soreness, constipation alternating with diarrhea.

WARNINGS:

If pregnant or breast-feeding, ask a health care professional before use.

Keep out of reach of children. In case of overdose, get medical help or contact a Poison Control Center right away.

Do not use if tamper evident seal is broken or missing.

Store in cool, dry place.

Keep out of reach of children. In case of overdose, get medical help or contact a Poison Control Center right away.

DIRECTIONS:

10 drops orally, 3 times a day. Consult a physician for use in children under 12 years of age.

INDICATIONS:

For temporary relief of abdominal bloating, & soreness, constipation alternating with diarrhea.

INACTIVE INGREDIENTS:

Demineralized Water, 25% Ethanol

QUESTIONS:

Distributed by:
BioActive Nutritional, Inc.
1803 N. Wickham Rd.
Melbourne, FL 32935
bioactivenutritional.com

PACKAGE LABEL DISPLAY:

BIOActive Nutritional

HEPATAPLEX

HOMEOPATHIC

1 FL OZ (30 ml)